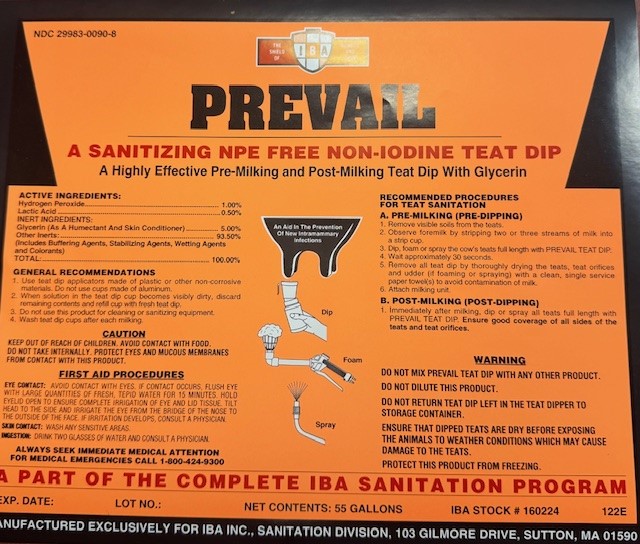 DRUG LABEL: PREVAIL
NDC: 29983-0090 | Form: SOLUTION
Manufacturer: IBA
Category: animal | Type: OTC ANIMAL DRUG LABEL
Date: 20241231

ACTIVE INGREDIENTS: HYDROGEN PEROXIDE 10.0 g/1 L; LACTIC ACID 5.0 g/1 L
INACTIVE INGREDIENTS: PHOSPHONIC ACID; SODIUM HYDROXIDE

PREVAIL A SANITIZING NPE FREE NON-IODINE TEAT DIP
A HIGHLY EFFECTIVE PRE-MILKING AND POST-MILKING TEAT DIP WITH GLYCERIN

ACTIVE INGREDIENT

Hydrogen Peroxide...........1.00%

Lactic Acid........................0.50%
INERT INGREDIENTS
Glycerin..........................5.00%
Other Inerts.....93.50%
(Includes Buffering Agents, Stabilizing Agents,Wetting Agents and Colorants)
Total.................100%

INDICATIONS AND USAGE

GENERAL RECOMMENDATIONS
1. Use teat dip applicators made of plastic or other non-corrosive materials. Do not use cups made of aluminum.
2. When solution in the teat dip cup becomes dirty and/or noticeably loses color, discard remaining contents and refill cup with fresh teat dip.
3. Do not use this product for cleaning or sanitizing equipment
4. Wash Teat Dip cups after each milking.
RECOMMENDED PROCEDURES FOR TEAT SANITATION
A. PRE-MILKING (PRE-DIPPING)
1. REMOVE VISIBLE SOILS FROM THE TEATS.
2. OBSERVE FOREMILK BY STRIPPING TWO OR THREE STREAMS OF MILK INTO A STRIP CUP.
3. DIP OR SPRAY THE COW'S TEATS FULL LENGTH WITH PREVAIL TEAT DIP.
4 WAIT APPROXIMATELY 30 SECONDS.
5. REMOVE ALL TEAT DIP BY THOROUGHLY DRYING THE TEATS AND TEAT ORIFICES AND UDDER (IF SPRAYING), WITH A CLEAN, SINGLE SERVICE PAPER TOWEL(S).
6. ATTACH MILKING UNIT
B. POST-MILKING (POST DIPPING)
Immediately after milking dip or spray all teats full length with PREVAIL Teat Dip Ensure good coverage of all sides of the teats and teat orifices.

WARNING

DO NOT MIX PREVAIL TEAP DIP WITH ANY OTHER PRODUCT

DO NOT DILUET THIS PRODUCT

DO NOT RETURN TEAT DIP LEFT IN THE TEAT DIPPER TO STORAGE CONTAINER
ENSURE THAT DIPPED TEATS ARE DRY BEFORE EXPOSING THE ANIMALS TO WEATHER CONDITIONS WHICH MAY CAUSE DAMAGE TO THE TEATS.
PROTECT THIS PRODUCT FROM FREEZING.

CAUTION: KEEP OUT OF REACH OF CHILDREN.
AVOID CONTACT WITH FOOD. DO NOT TAKE INTERNALLY.

FIRST AID PROCEDURES

EYE CONTACT: AVOID CONTACT WITH EYES. IF CONTACT OCCURS, FLUSH EYE WITH LARGE QUANTITIES OF FRESH, TEPID WATER FOR 15 MINUTES. HOLD EYELID OPEN TO ENSURE COMPLETE IRRIGATION OF EYE AND LID TISSUE. TILT HEAD TO THE SIDE AND IRRIGATE THE EYE FROM THE BRIDGE OF THE NOSE TO THE OUTSIDE OF THE FACE. IF IRRITATION DEVELOPS, CONSULT A PHYSICIAN.

SKIN CONTACT: WASH ANY SENSITIVE AREAS.

INGESTION: DRINK TWO GLASSES OF WATER AND CONSULT A PHYSICIAN.

ALWAYS SEEK IMMEDIATE MEDICAL ATTENTION

FOR MEDICAL EMERGENCIES CALL 1-800-424-9300